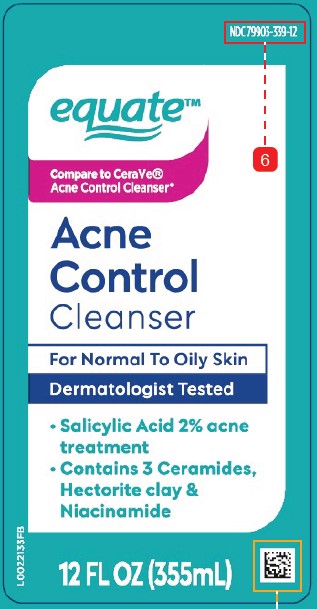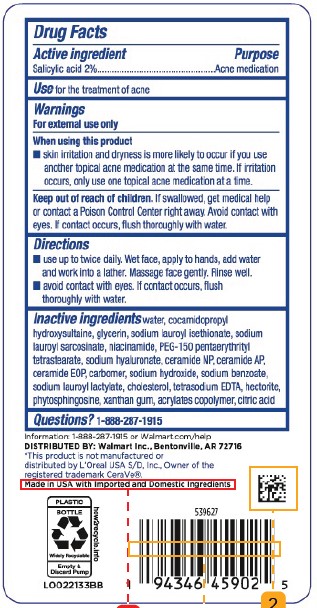 DRUG LABEL: Acne Control Cleanser
NDC: 79903-339 | Form: LIQUID
Manufacturer: Walmart Inc.
Category: otc | Type: HUMAN OTC DRUG LABEL
Date: 20260227

ACTIVE INGREDIENTS: SALICYLIC ACID 20 mg/1 mL
INACTIVE INGREDIENTS: WATER; COCAMIDOPROPYL HYDROXYSULTAINE; GLYCERIN; SODIUM LAUROYL ISETHIONATE; SODIUM LAUROYL SARCOSINATE; NIACINAMIDE; PEG-150 PENTAERYTHRITYL TETRASTEARATE; HYALURONATE SODIUM; CERAMIDE NP; CERAMIDE AP; CERAMIDE 1; CARBOMER HOMOPOLYMER, UNSPECIFIED TYPE; SODIUM HYDROXIDE; SODIUM BENZOATE; SODIUM LAUROYL LACTYLATE; CHOLESTEROL; EDETATE SODIUM; HECTORITE; PHYTOSPHINGOSINE; XANTHAN GUM; BUTYL ACRYLATE/METHYL METHACRYLATE/METHACRYLIC ACID COPOLYMER (18000 MW); CITRIC ACID

Equate 414.000/414AA
Acne Control Cleanser

ACTIVE INGREDIENT

Salicylic acid 2%

PURPOSE

Acne medication

Use

for the treatment of acne

Warnings

For external use only

When using this product

- skin irritation and dryness is more likely to occur if you use another topical acne medication at the same time. If irritation occurs, only use one topical acne medication at a time.

Keep out of reach of children.

If swallowed, get medical help or contact a Poison Control Center right away. Avoid contact with eyes. If contact occurs, flush thoroughly with water.

Directions

- use up to twice daily. Wet face, apply to hands, add water and work into a lather. Massage face gently. Rinse well.
- avoid contact with eyes. If contact occurs, flush thoroughly with water.

Inactive ingredients

water, cocamidopropyl hydroxysultaine, glycerin, sodium lauroyl isethionate, sodium lauroyl sarcosinate, niacinamide, PEG-150 pentaerythrityl tetrastearate, sodium hyaluronate, ceramide NP, ceramide AP, ceramide EOP, carbomer, sodium hydroxide, sodium benzoate, sodium lauroyl lactylate, cholesterol, tetrasodium EDTA, hectorite, phytosphingosine, xanthan gum, acrylates copolymer, citric acid

Questions?

1-888-287-1915

ADVERSE REACTION

Information: 1-888-287-1915 or Walmart.com/help

Distributed by: Walmart Inc., Bentonville, AR 72716

Made in USA with Imported and Domestic Ingredients

PLASTIC BOTTLE

Widely Recyclable

Empty & Discard Pump

how2recycle.info

Disclaimer

*This product is not manufactured or distributed by L'Oreal USA S/D, Inc., Owner of the registered trademark CeraVe.

PRINCIPAL DISPLAY PANEL

NDC 79903-339-12

equate™

Compare to CeraVe® Acne Control Cleanser*

ACNE CONTROL CLEANSER

For Normal To Oily Skin

Dermatologist Tested

- Salicyclic Acid 2% Acne Treatment
- Contains 3 ceramides, hectorite clay and niacinamide

12 FL OZ (355 mL)